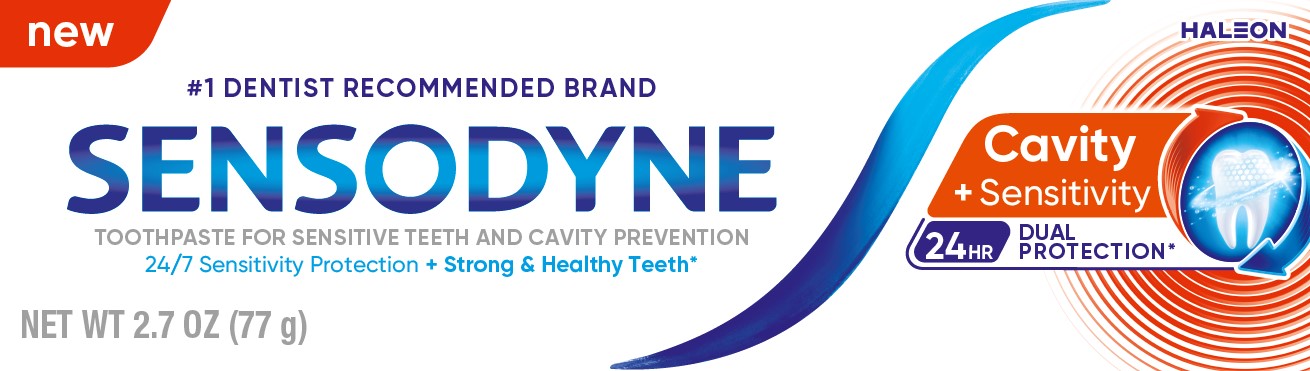 DRUG LABEL: Sensodyne

NDC: 0135-4032 | Form: PASTE, DENTIFRICE
Manufacturer: Haleon US Holdings LLC
Category: otc | Type: HUMAN OTC DRUG LABEL
Date: 20251124

ACTIVE INGREDIENTS: POTASSIUM NITRATE 50 mg/1 g; SODIUM FLUORIDE 1.5 mg/1 g
INACTIVE INGREDIENTS: WATER; SORBITOL; HYDRATED SILICA; GLYCERIN; COCAMIDOPROPYL BETAINE; XANTHAN GUM; TITANIUM DIOXIDE; SACCHARIN SODIUM; SODIUM HYDROXIDE

Drug Facts

Active ingredients

Potassium nitrate 5%

Sodium fluoride 0.25% (0.15% w/v fluoride ion)

Purposes

Antihypersensitivity

Anticavity

Uses

- builds increasing protection against painful sensitivity of the teeth to cold, heat, acids, sweets, or contact.
- aids in the prevention of dental cavities.

Warnings

Stop use and ask a dentist if

- the problem persists or worsens. Sensitive teeth may indicate a serious problem that may need prompt care by a dentist.
- pain/sensitivity still persists after 4 weeks of use.

Keep out of reach of children.

If more than used for brushing is accidentally swallowed, get medical help or contact a Poison Control Center right away.

Directions

- adults and children 12 years of age and older:
  - apply at least a 1-inch strip of the product onto a soft bristle toothbrush.
  - brush teeth thoroughly for at least 1 minute twice a day (morning and evening), or as recommended by a dentist or doctor. Make sure to brush all sensitive areas of the teeth.
    Minimize swallowing.
- children under 12 years of age:Consult a dentist or doctor.

Other information

- do not store above 25˚C (77˚F)

Inactive ingredients

water, sorbitol, hydrated silica, glycerin, cocamidopropyl betaine, flavor, xanthan gum, titanium dioxide, sodium saccharin, sodium hydroxide

Questions or comments?

1-866-844-2797

Additional Information

ALWAYS FOLLOW THE LABEL

Specifically formulated to enhance remineralization, which strengthens the tooth’s surface*

Cavities + Sensitivity in teeth are common dental problems

Contains optimized fluoride technology to draw minerals into the tooth structure to help protect against cavities*

*with continued twice daily brushing

Potassium nitrate provides clinically proven long lasting sensitivity protection*

24 HRDUAL PROTECTION FROM CAVITIES & SENSITIVITY* + EVERYDAY FRESHNESS

Principal Display Panel

new

#1 DENTIST RECOMMENDED BRAND

SENSODYNE

TOOTHPASTE FOR SENSITIVE TEETH AND CAVITY PREVENTION

24/7 Sensitivity Protection + Strong & Healthy Teeth*

Cavity + Sensitivity 24 HR DUAL PROTECTION*

NET WT 2.7 OZ (77 g)